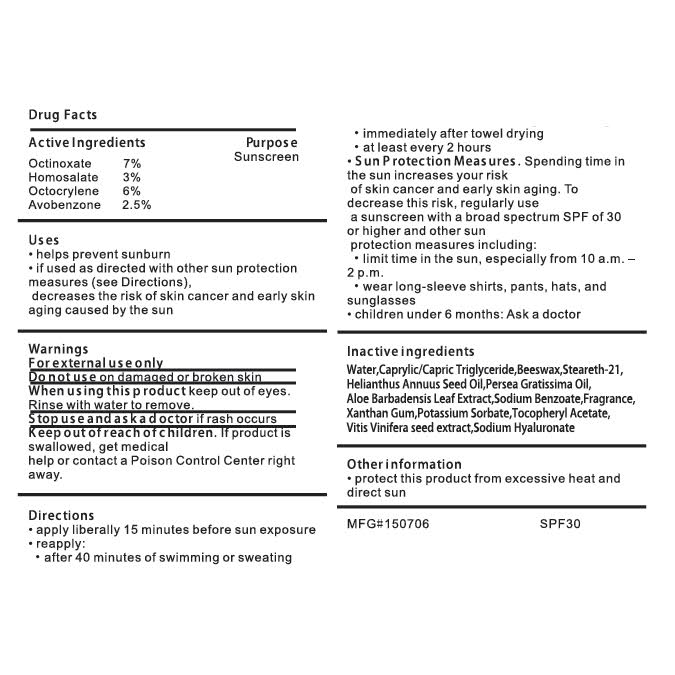 DRUG LABEL: White Girl Sunscreen
NDC: 70641-111 | Form: LOTION
Manufacturer: White Girl, LLC
Category: otc | Type: HUMAN OTC DRUG LABEL
Date: 20170116

ACTIVE INGREDIENTS: OCTINOXATE 7 g/100 g; AVOBENZONE 2.5 g/100 g; OCTOCRYLENE 6 g/100 g; HOMOSALATE 3 g/100 g
INACTIVE INGREDIENTS: STEARETH-21 1.5 g/100 g

White Girl Sunscreen

Active Ingredients

Octinoxate 7%

Homosalate 3%

Octocrylene 6%

Avobenzone 2.5%

Drug Facts

Uses

- helps prevent sunburn
- if used as directed with other sun protection measures (see Directions)
- decreases the risk of skin cancer and early skin aging caused by sun

Warnings

For external use only

Do not use on damaged or broken skin

When using this product keep out of eyes.

Rinse with water to remove.

Stop use and ask a doctor if rash occurs

Keep out of reach of children. If product is swallowed, get medical help

or contact a Poison Control Center right away.

Directions

- apply liberally 15 minutes before sun exposure
- reapply:
- after 40 minutes of swimming or sweating
- immediately after towel drying
- at least every 2 hours
- Sun Protection Measures. Spending time in the sun increasess your risk of skin cancer and early skin aging. To decrease this risk, regularly use a sunscreen with a broad spectrum spf of 30 or higher and other sun protection measures including:
- limit time in the sun, especially from 10 a.m-2 p.m.
- wear long-sleeve shirts, pants, hats, and sunglasses
- children under 6 months: Ask a doctor

Other Information

protect this product from excessive heat and direct sun

White Girl Sunscreen 30 SPF

www.whitegirlsunscreen.com